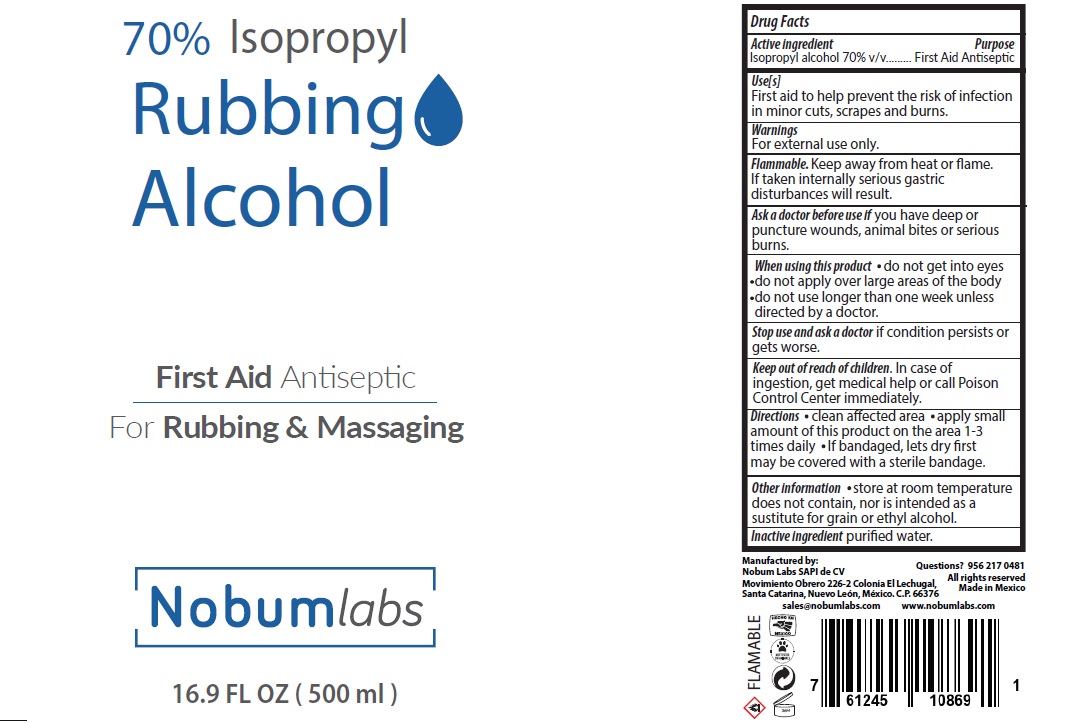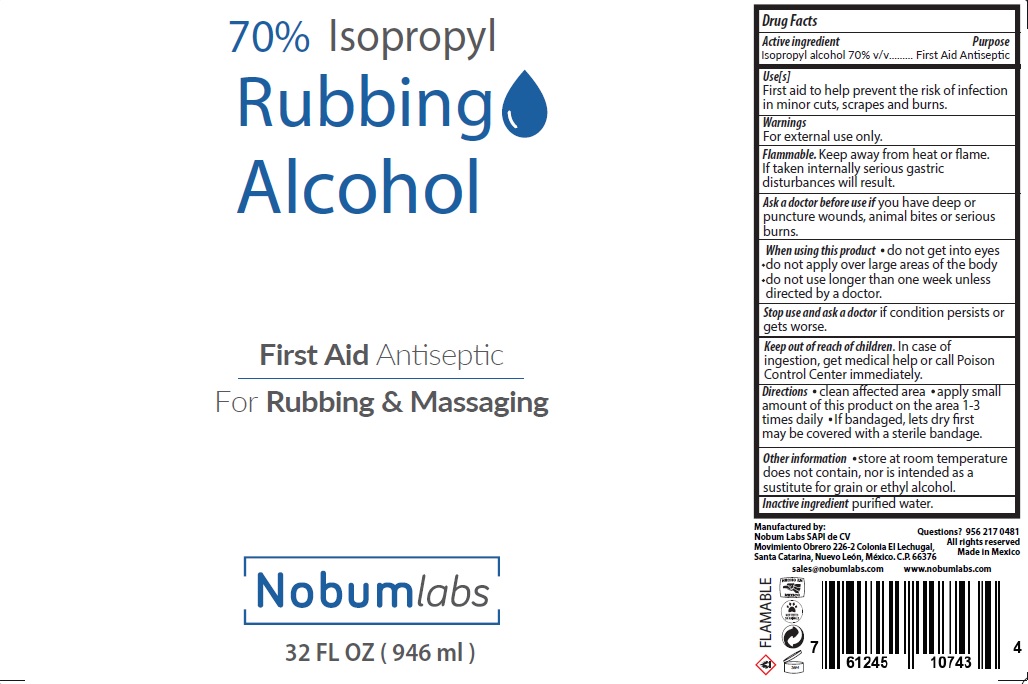 DRUG LABEL: Rubbing Alcohol
NDC: 81213-001 | Form: LIQUID
Manufacturer: Nobum Labs, S.A.P.I. de C.V.
Category: otc | Type: HUMAN OTC DRUG LABEL
Date: 20220127

ACTIVE INGREDIENTS: ISOPROPYL ALCOHOL 70 mL/100 mL
INACTIVE INGREDIENTS: WATER 30 mL/100 mL

Rubbing Alcohol (IPA)

Active Ingredient(s)

Isopropyl Alcohol 70% v/v. Purpose: First Aid Antiseptic

Purpose

First Aid Antiseptic

Use

First aid to help prevent the risk of infection in minor cuts, scrapes, and burns.

Warnings

For external use only.

Keep away from heat or flame. If taken internally serious gastric disturbances will result.

Ask a doctor before use if you have deep or puncture wounds, animal bites or serious burns.

WHEN USING

* do not get into eyes.

* do not apply over large areas of the body.
*do not use longer than one week unless directed by a doctor.

Stop use and ask a doctor if condition persists or gets worse.

KEEP OUT OF REACH OF CHILDREN

In case of ingestion, get medical help or call Poison Control Center immediately.

Directions

* clean affected area

*apply small amount of this product on the area 1-3 times daily

* If bandaged, lets dry first may be covered with a sterile bandage

Other information

store at room temperature does not contain, nor is intended as a sustitute for grain or ethyl alcohol.

Inactive ingredients

purified water.

Package Label - Principal Display Panel 500 ml NDC: 81213-001-01

500 ml NDC: 81213-001-01

946 mL NDC: 81213-001-02